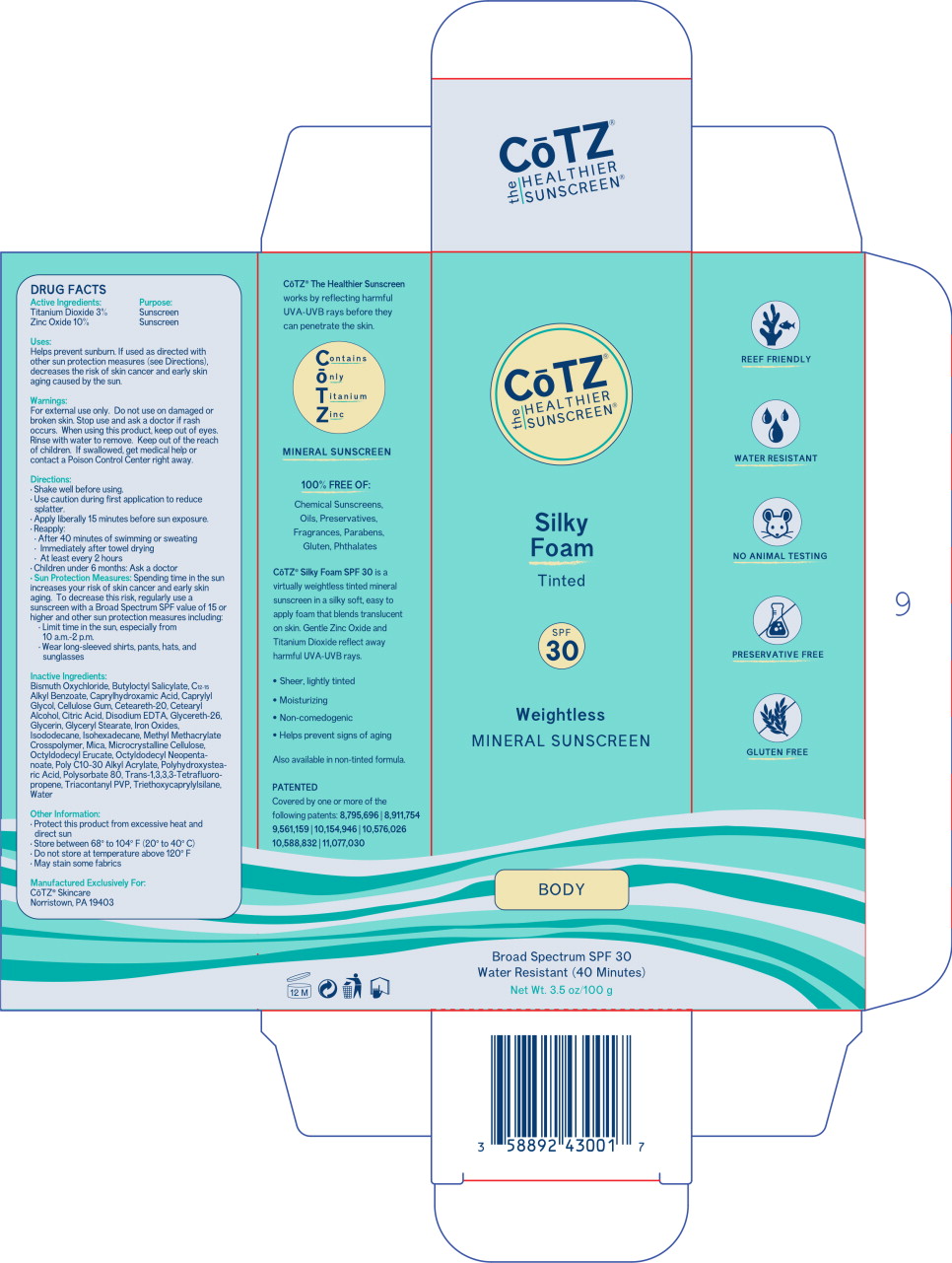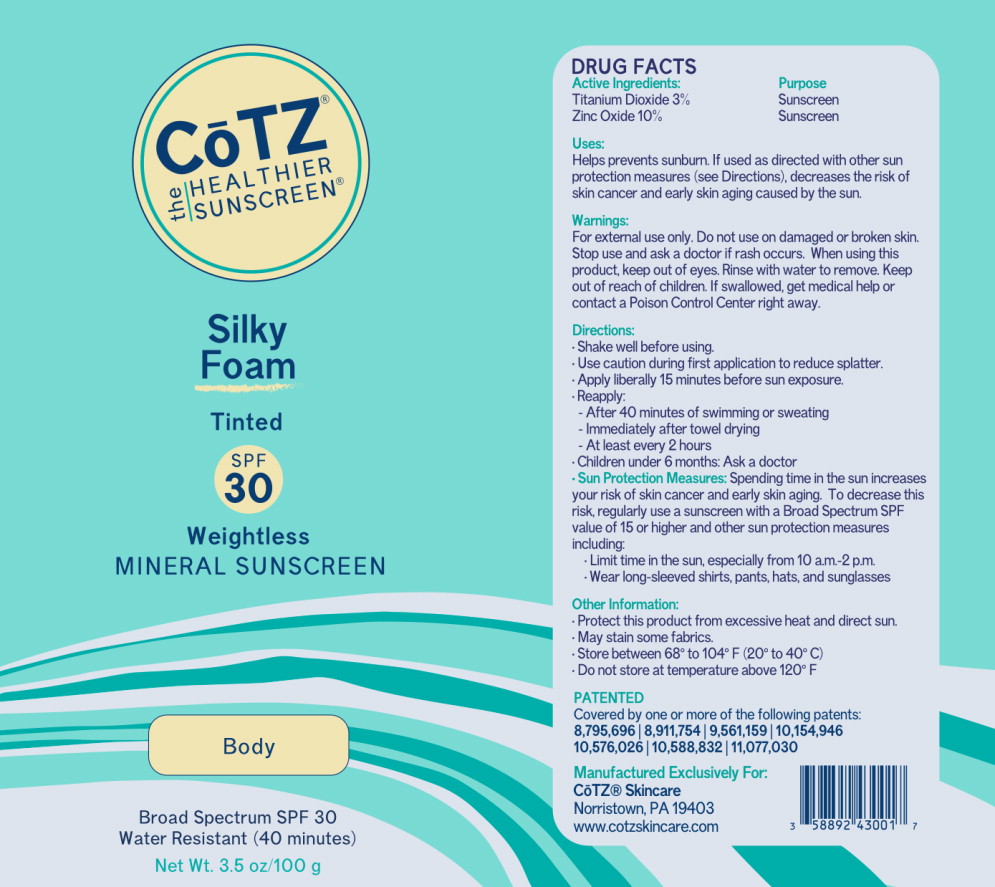 DRUG LABEL: CoTZ Silky Foam - Tinted
NDC: 58892-430 | Form: AEROSOL, FOAM
Manufacturer: Fallien Cosmeceuticals, LTD
Category: otc | Type: HUMAN OTC DRUG LABEL
Date: 20250124

ACTIVE INGREDIENTS: Titanium Dioxide 30 mg/1 g; Zinc Oxide 100 mg/1 g
INACTIVE INGREDIENTS: BEHENYL ACRYLATE POLYMER; BISMUTH OXYCHLORIDE; BUTYLOCTYL SALICYLATE; ALKYL (C12-15) BENZOATE; CAPRYLHYDROXAMIC ACID; CAPRYLYL GLYCOL; CARBOXYMETHYLCELLULOSE SODIUM, UNSPECIFIED FORM; POLYOXYL 20 CETOSTEARYL ETHER; CETOSTEARYL ALCOHOL; CITRIC ACID MONOHYDRATE; EDETATE DISODIUM ANHYDROUS; GLYCERETH-26; GLYCERIN; GLYCERYL MONOSTEARATE; FERRIC OXIDE RED; FERRIC OXIDE YELLOW; FERROSOFERRIC OXIDE; ISODODECANE; ISOHEXADECANE; METHYL METHACRYLATE/GLYCOL DIMETHACRYLATE CROSSPOLYMER; MICA; MICROCRYSTALLINE CELLULOSE; OCTYLDODECYL NEOPENTANOATE; POLYHYDROXYSTEARIC ACID (2300 MW); POLY(METHYL METHACRYLATE; 450000 MW); POLYSORBATE 80; OCTYLDODECYL ERUCATE; 1,3,3,3-TETRAFLUOROPROPENE, (1E)-; TRICONTANYL POVIDONE; TRIETHOXYCAPRYLYLSILANE; WATER

Drug Facts

Active Ingredients:

Titanium Dioxide 3%

Zinc Oxide 10%

Purpose:

Sunscreen

Sunscreen

Uses:

Helps prevent sunburn. If used as directed with other sun protection measures (see directions), decreases the risk of skin cancer and early skin aging caused by the sun.

Warnings:

For external use only. Do not use on damaged or broken skin. Stop use and ask a doctor if rash occurs.

When using this product, keep out of eyes. Rinse with water to remove. Keep out of the reach of children. If swallowed, get medical help or contact a Poison Control Center right away.

Directions:

- Shake well before using.
- Use caution during 1st application to reduce splatter.
- Apply liberally 15 minutes before sun exposure.
- Reapply:
  - After 40 minutes of swimming or sweating
  - Immediately after towel drying
  - At least every 2 hours
  - Children under 6 months: Ask a doctor
- Sun Protection Measures: Spending time in the sun increases your risk of skin cancer and early skin aging. To decrease this risk, regularly use a sunscreen with a Broad Spectrum SPF value of 15 or higher and other sun protection measures including:
  - Limit time in the sun, especially from 10 a.m.-2 p.m.
  - Wear long-sleeved shirts, pants, hats, and sunglasses

Inactive Ingredients:

Bismuth Oxychloride, Butyloctyl Salicylate, C12-15 Alkyl Benzoate, Caprylhydroxamic Acid, Caprylyl Glycol, Cellulose Gum, Ceteareth-20, Cetearyl Alcohol, Citric Acid, Disodium EDTA, Glycereth-26, Glycerin, Glyceryl Stearate, Iron Oxides, Isododecane, Isohexadecane, Methyl Methacrylate Crosspolymer, Mica, Microcrystalline Cellulose, Octyldodecyl Ecruate, Octyldodecyl Neopentanoate, Poly C10-30 Alkyl Acrylate, Polyhydroxystearic Acid, Polysorbate 80, Trans-1,3,3,3-Tetrafluoropropene, Triacontanyl PVP, Triethoxycaprylylsilane, Water

Other Information:

- Protect this product from excessive heat and direct sun
- May stain some fabrics
- Store between 68° to 104°F (20° to 40° C)
- DO not store at temperature above 120° F

Manufactured Exclusively For:
CoTZ® Skincare
Norristown, PA 19403
www.cotzskincare.com

Principal Display Panel – Carton Label

CoTZ®
the HEALTHIER SUNSCREEN®

Silky
Foam

Tinted

SPF
30

Vanishing Zinc Oxide
MINERAL SUNCREEN

BODY

Broad Spectrum SPF 30

Water Resistant (40 Minutes)

Net Wt. 3.5 oz/100 g

Principal Display Panel – Can Label

CoTZ®
the HEALTHIER SUNSCREEN®

Silky
Foam

Tinted

SPF
30

Foaming
MINERAL SUNSCREEN

BODY

Broad Spectrum SPF 30

Water Resistant (40 Minutes)

Net Wt. 3.5 oz/100 g